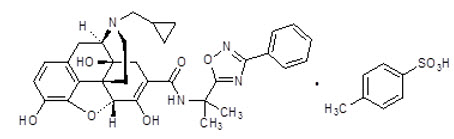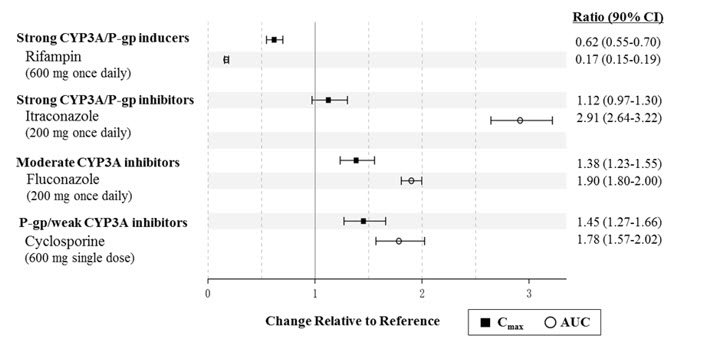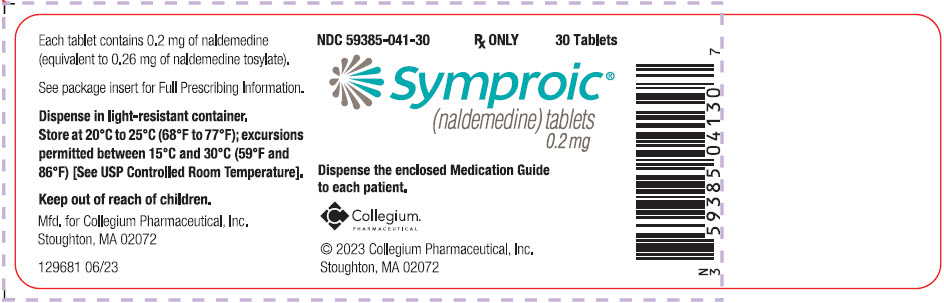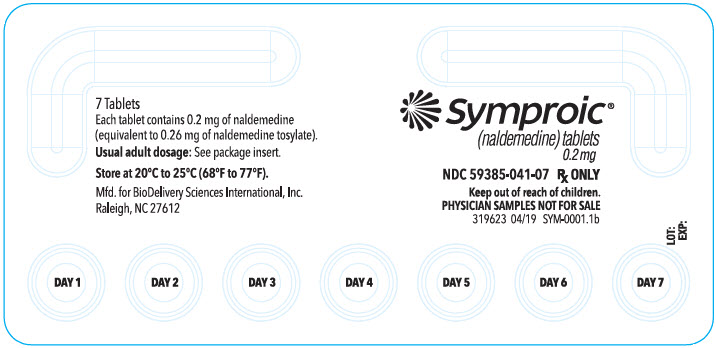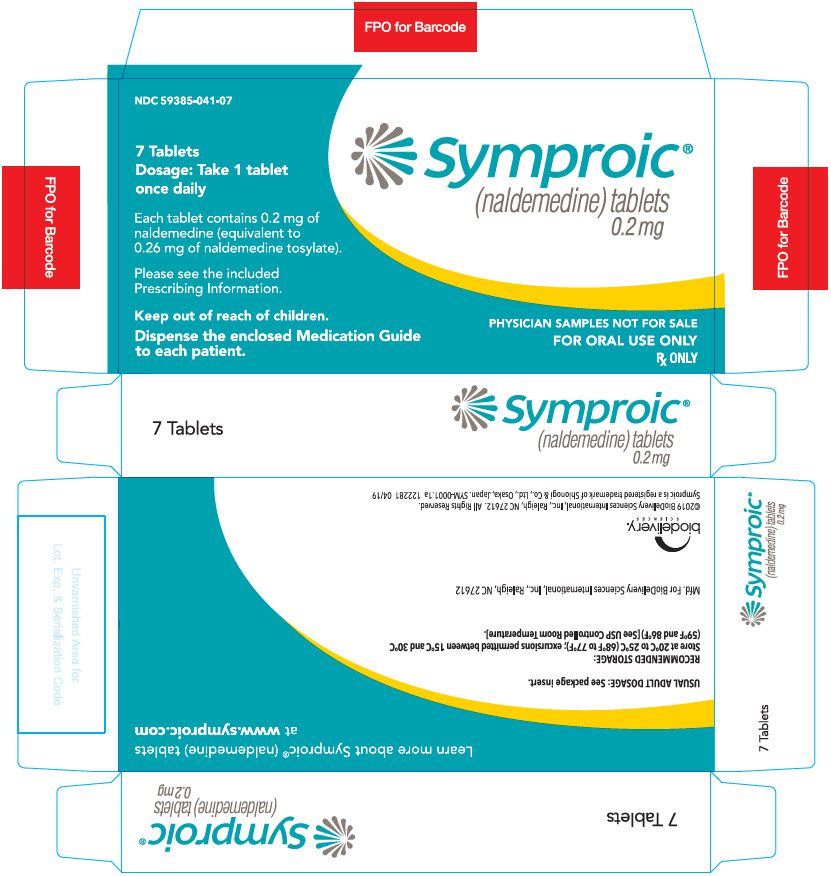 DRUG LABEL: SYMPROIC
NDC: 59385-041 | Form: TABLET
Manufacturer: BioDelivery Sciences International Inc
Category: prescription | Type: HUMAN PRESCRIPTION DRUG LABEL
Date: 20250725

ACTIVE INGREDIENTS: naldemedine tosylate 0.2 mg/1 1
INACTIVE INGREDIENTS: Mannitol; Croscarmellose Sodium; Magnesium Stearate; Hypromellose, Unspecified; Talc; Ferric Oxide Yellow

HIGHLIGHTS OF PRESCRIBING INFORMATION

These highlights do not include all the information needed to use SYMPROIC safely and effectively. See full prescribing information for SYMPROIC.
SYMPROIC® (naldemedine tablets for oral use)
Initial U.S. Approval: 2017

RECENT MAJOR CHANGES

Warnings and Precautions, Gastrointestinal Perforation (5.1) | 07/2025

1 INDICATIONS AND USAGE

SYMPROIC is an opioid antagonist indicated for the treatment of opioid-induced constipation (OIC) in adult patients with chronic non-cancer pain, including patients with chronic pain related to prior cancer or its treatment who do not require frequent (e.g., weekly) opioid dosage escalation (1)

2 DOSAGE AND ADMINISTRATION

Administration (2.1):

- Alteration of analgesic dosing regimen prior to initiating SYMPROIC is not required
- Patients receiving opioids for less than 4 weeks may be less responsive to SYMPROIC
- Discontinue SYMPROIC if treatment with the opioid pain medication is also discontinued

Dosage (2.2):

- In adults, the recommended dosage is 0.2 mg once daily with or without food

3 DOSAGE FORMS AND STRENGTHS

Tablets: 0.2 mg naldemedine (3)

4 CONTRAINDICATIONS

- Patients with known or suspected gastrointestinal obstruction or at increased risk of recurrent obstruction (4, 5.1)
- Patients with a history of a hypersensitivity reaction to naldemedine (6.1)

5 WARNINGS AND PRECAUTIONS

- Gastrointestinal perforation: Consider the overall risk benefit in patients with known or suspected lesions of the GI tract. Monitor for severe, persistent, or worsening abdominal pain; discontinue if development of symptoms (5.1)
- Opioid withdrawal: Consider the overall risk benefit in patients with disruptions to the blood-brain barrier. Monitor symptoms of opioid withdrawal (5.2)

6 ADVERSE REACTIONS

Most common adverse reactions (≥2%) are: abdominal pain, diarrhea, nausea and gastroenteritis (6.1)

To report SUSPECTED ADVERSE REACTIONS, contact BioDelivery Sciences International, Inc. at 1-800-469-0261 or FDA at 1-800-FDA-1088 or www.fda.gov/medwatch.

7 DRUG INTERACTIONS

- Strong CYP3A inducers (e.g., rifampin): Decreased naldemedine concentrations; avoid concomitant use (7)
- Other opioid antagonists: Potential for additive effect and increased risk of opioid withdrawal; avoid concomitant use (7)
- Moderate (e.g., fluconazole) and strong (e.g., itraconazole) CYP3A4 inhibitors: Increased naldemedine concentrations; monitor for adverse reactions (7)
- P-gp inhibitors (e.g., cyclosporine): Monitor for adverse reactions (7)

8 USE IN SPECIFIC POPULATIONS

- Pregnancy: May precipitate opioid withdrawal in a fetus (8.1)
- Lactation: Discontinue drug or breastfeeding taking into consideration importance of drug to mother (8.2)
- Hepatic Impairment: Avoid in severe impairment (8.6)

FULL PRESCRIBING INFORMATION

1 INDICATIONS AND USAGE

SYMPROIC is indicated for the treatment of opioid-induced constipation (OIC) in adult patients with chronic non-cancer pain, including patients with chronic pain related to prior cancer or its treatment who do not require frequent (e.g., weekly) opioid dosage escalation.

2 DOSAGE AND ADMINISTRATION

2.1 Administration

- Alteration of analgesic dosing regimen prior to initiating SYMPROIC is not required.
- Patients receiving opioids for less than 4 weeks may be less responsive to SYMPROIC [see Clinical Studies (14)].
- Discontinue SYMPROIC if treatment with the opioid pain medication is also discontinued.

2.2 Adult Dosage

The recommended dosage of SYMPROIC is 0.2 mg orally once daily with or without food.

3 DOSAGE FORMS AND STRENGTHS

Tablets: 0.2 mg naldemedine; supplied as yellow, round, film-coated, debossed with Shionogi marking above the identifier code 222 on one side and 0.2 on the other side.

4 CONTRAINDICATIONS

SYMPROIC is contraindicated in:

- Patients with known or suspected gastrointestinal obstruction and patients at increased risk of recurrent obstruction, due to the potential for gastrointestinal perforation [see Warnings and Precautions (5.1)].
- Patients with a history of a hypersensitivity reaction to naldemedine. Reactions have included bronchospasm and rash [see Adverse Reactions (6.1)].

5 WARNINGS AND PRECAUTIONS

5.1 Gastrointestinal Perforation

Cases of gastrointestinal (GI) perforation have been reported with use of another peripherally acting opioid antagonist, including SYMPROIC. Postmarketing cases of GI perforation, including fatal cases, were reported when SYMPROIC was used in patients at risk of GI perforation (e.g., GI cancer, past GI surgery, diverticulitis, chemotherapy/radiation). SYMPROIC is contraindicated in patients with known or suspected gastrointestinal obstruction or in patients at risk of recurrent obstruction. Take into account the overall risk-benefit profile when using SYMPROIC in patients with these conditions or other conditions which might result in impaired integrity of the gastrointestinal tract wall (e.g., Crohn's disease). Monitor for the development of severe, persistent, or worsening abdominal pain; discontinue SYMPROIC in patients who develop this symptom.

5.2 Opioid Withdrawal

Clusters of symptoms consistent with opioid withdrawal, including hyperhidrosis, chills, increased lacrimation, hot flush/flushing, pyrexia, sneezing, feeling cold, abdominal pain, diarrhea, nausea, and vomiting have occurred in patients treated with SYMPROIC [see Adverse Reactions (6.1)].

Patients having disruptions to the blood-brain barrier may be at increased risk for opioid withdrawal or reduced analgesia. Take into account the overall risk-benefit profile when using SYMPROIC in such patients. Monitor for symptoms of opioid withdrawal in such patients.

6 ADVERSE REACTIONS

Serious and important adverse reactions described elsewhere in labeling include:

- Gastrointestinal perforation [see Warnings and Precautions (5.1)]
- Opioid withdrawal [see Warnings and Precautions (5.2)]

6.1 Clinical Trials Experience

Because clinical trials are conducted under widely varying conditions, adverse reaction rates observed in the clinical trials of a drug cannot be directly compared to rates in the clinical trials of another drug and may not reflect the rates observed in practice.

The data described below reflect exposure to SYMPROIC in 1163 patients in clinical trials, including 487 patients with exposures greater than six months and 203 patients with exposures of 12 months.

The following safety data are derived from three double-blind, placebo-controlled trials in patients with OIC and chronic non-cancer pain: two 12-week studies (Studies 1 and 2) and one 52-week study (Study 3) [see Clinical Studies (14)].

In Studies 1 and 2, patients on laxatives were required to discontinue their use prior to study enrollment. All patients were restricted to bisacodyl rescue treatment during the study. In Study 3, approximately 60% of patients in both treatment groups were on a laxative regimen at baseline; patients were allowed to continue using their laxative regimen throughout the study duration. The safety profile of SYMPROIC relative to placebo was similar regardless of laxative use.

Tables 1 and 2 list common adverse reactions occurring in at least 2% of patients receiving SYMPROIC and at an incidence greater than placebo. Table 1 shows pooled 12-week data from Studies 1 and 2. Table 2 shows 12-week data from Study 3.

Table 1: Common Adverse Reactions [Adverse reactions occurring in at least 2% of patients receiving SYMPROIC and at an incidence greater than placebo] in Patients with OIC and Chronic Non-Cancer Pain (12-week data from Studies 1 and 2)
Adverse Reaction | SYMPROIC 0.2 mg once daily N=542 | Placebo N=546
Abdominal pain [Abdominal pain includes abdominal discomfort, abdominal pain, abdominal pain lower, abdominal pain upper, gastrointestinal pain.] | 8% | 2%
Diarrhea | 7% | 2%
Nausea | 4% | 2%
Gastroenteritis | 2% | 1%

Table 2: Common Adverse Reactions [Adverse reactions occurring in at least 2% of patients receiving SYMPROIC and at an incidence greater than placebo] in Patients with OIC and Chronic Non-Cancer Pain (12-week data from Study 3)
Adverse Reaction | SYMPROIC 0.2 mg once daily N=621 | Placebo N=619
Abdominal pain [Abdominal pain includes abdominal discomfort, abdominal pain, abdominal pain lower, abdominal pain upper.] | 11% | 5%
Diarrhea | 7% | 3%
Nausea | 6% | 5%
Vomiting | 3% | 2%
Gastroenteritis | 3% | 1%

Adverse reactions up to 12 months in Study 3 are similar to those listed in Tables 1 and 2 (diarrhea: 11% vs. 5%, abdominal pain: 8% vs. 3%, and nausea: 8% vs. 6% for SYMPROIC and placebo, respectively).

Opioid Withdrawal

In Studies 1, 2 and 3, adverse reactions consistent with opioid withdrawal were based on investigator assessment and adjudicated based upon the occurrence of at least 3 adverse reactions potentially related to opioid withdrawal with onset of a constellation of those symptoms occurring on the same day or within one day of each other.

Adverse reactions of possible opioid withdrawal could include non-gastrointestinal (GI) symptoms (e.g., hyperhidrosis, hot flush or flushing, chills, tremor, tachycardia, anxiety, agitation, yawning, rhinorrhea, increased lacrimation, sneezing, feeling cold, and pyrexia), GI symptoms (e.g., vomiting, diarrhea, or abdominal pain), or both GI and non-GI symptoms.

In pooled Studies 1 and 2, the incidence of adverse reactions of opioid withdrawal was 1% (8/542) for SYMPROIC and 1% (3/546) for placebo. In Study 3 (52-week data), the incidence was 3% (20/621) for SYMPROIC and 1% (9/619) for placebo. Most SYMPROIC treated subjects experienced nearly equal incidence of GI only or both GI and non-GI symptoms.

Less Common Adverse Reactions:

Two patients developed symptoms of hypersensitivity following a single dose of SYMPROIC. One patient reported bronchospasm and another rash.

6.2 Postmarketing Experience

The following adverse reactions have been identified during post-approval use of SYMPROIC. Because reactions are reported voluntarily from a population of uncertain size, it is not always possible to reliably estimate the frequency or establish a causal relationship to drug exposure.

Gastrointestinal disorders: Gastrointestinal perforation [see Warnings and Precautions (5.1)].

7 DRUG INTERACTIONS

Table 3 includes drugs with clinically important drug interactions with SYMPROIC and instructions for preventing or managing the interaction.

Table 3: Clinically Relevant Interactions Affecting Naldemedine When Co-Administered with Other Drugs
Strong CYP3A Inducers (e.g., rifampin, carbamazepine, phenytoin, St. John's Wort)
Clinical Impact | Significant decrease in plasma naldemedine concentrations, which may reduce efficacy [see Clinical Pharmacology (12.3)]
Intervention | Avoid use of SYMPROIC with strong CYP3A inducers.
Other Opioid Antagonists
Clinical Impact | Potential for additive effect of opioid receptor antagonism and increased risk of opioid withdrawal.
Intervention | Avoid use of SYMPROIC with another opioid antagonist.
Moderate (e.g., fluconazole, atazanavir, aprepitant, diltiazem, erythromycin) and Strong (e.g., itraconazole, ketoconazole, clarithromycin, ritonavir, saquinavir) CYP3A Inhibitors
Clinical Impact | Increase in plasma naldemedine concentrations [see Clinical Pharmacology (12.3)]
Intervention | Monitor for potential naldemedine-related adverse reactions [see Adverse Reactions (6.1)].
P-glycoprotein (P-gp) Inhibitors (e.g., amiodarone, captopril, cyclosporine, quercetin, quinidine, verapamil)
Clinical Impact | Increase in plasma naldemedine concentrations [see Clinical Pharmacology (12.3)]
Intervention | Monitor for potential naldemedine-related adverse reactions [see Adverse Reactions (6.1)].

8 USE IN SPECIFIC POPULATIONS

8.1 Pregnancy

Risk Summary

There are no available data with naldemedine in pregnant women to inform a drug-associated risk of major birth defects and miscarriage. There is a potential for opioid withdrawal in a fetus when SYMPROIC is used in pregnant women [see Clinical Considerations]. SYMPROIC should be used during pregnancy only if the potential benefit justifies the potential risk.

In a rat embryo-fetal development study following oral administration of naldemedine during the period of organogenesis at doses resulting in systemic exposure approximately 23,000 times the human area under the plasma-concentration time curve (AUC) at the recommended human dose of 0.2 mg/day, no developmental abnormalities were observed. In rabbits, there were no adverse effects on embryo-fetal development following oral administration of naldemedine during the period of organogenesis at doses resulting in systemic exposure approximately 226 times the human AUC at the recommended human dose of 0.2 mg/day [see Data]. No effects on pre- and postnatal development were observed in rats at exposures 12 times human exposures at the recommended human dose.

The estimated background risk of major birth defects and miscarriage for the indicated population is unknown. In the U.S. general population, the estimated background risk of major birth defects and miscarriage in clinically recognized pregnancies is 2 to 4% and 15 to 20%, respectively.

Clinical Considerations

Fetal/Neonatal Adverse Reactions

Naldemedine crosses the placenta, and may precipitate opioid withdrawal in a fetus due to the immature fetal blood-brain barrier.

Data

Animal Data

In rats, there were no adverse effects on embryo-fetal development following oral administration of naldemedine during the period of organogenesis at doses up to 1000 mg/kg/day (approximately 23,000 times the human exposures (AUC) at the recommended human dose). In rabbits, there were no adverse effects on embryo-fetal development following oral administration of naldemedine during the period of organogenesis at doses up to 100 mg/kg/day (approximately 226 times the human exposures (AUC) at the recommended human dose). At 400 mg/kg/day (approximately 844 times the human exposures (AUC) at the recommended human dose), effects in maternal animals included body weight loss/decreased body weight gain and food consumption, fetal loss, and premature delivery. Decreased fetal body weights at this dose may be related to the maternal toxicity observed.

In the pre- and postnatal development study, pregnant rats were administered naldemedine at oral doses up to 1000 mg/kg/day from gestation day 7 through lactation day 20. No effects on pre- and postnatal development were observed in rats at 1 mg/kg/day (approximately 12 times the human exposures (AUC) at the recommended human dose). A single dam died at parturition at 1000 mg/kg/day, and decreased body weights/body weight gain and food consumption, poor nursing, and total litter loss were noted at 30 and 1000 mg/kg/day (approximately 626 and 17,000 times the human exposures (AUC) at the recommended human dose, respectively). Decreases in the offspring viability index on Day 4 after birth were noted at 30 and 1000 mg/kg/day, and low body weights and delayed pinna unfolding in pups were noted at 1000 mg/kg/day.

8.2 Lactation

Risk Summary

There is no information regarding the presence of naldemedine in human milk, the effects on the breastfed infant, or the effects on milk production. Naldemedine was present in the milk of rats [see Data]. Because of the potential for serious adverse reactions, including opioid withdrawal in breastfed infants, a decision should be made to discontinue breastfeeding or discontinue the drug, taking into account the importance of the drug to the mother. If drug is discontinued in order to minimize drug exposure to a breastfed infant, advise women that breastfeeding may be resumed 3 days after the final dose of SYMPROIC.

Data

Drug-related radioactivity was transferred into milk of lactating rats following a single oral dose of 1 mg/kg [carbonyl-^14C]-naldemedine.

8.4 Pediatric Use

The safety and effectiveness of SYMPROIC have not been established in pediatric patients.

8.5 Geriatric Use

Of the 1163 patients exposed to SYMPROIC in clinical studies, 183 (16%) were 65 years of age and over, while 37 (3%) were 75 years and over. No overall differences in safety or effectiveness between these and younger patients were observed, but greater sensitivity of some older individuals cannot be ruled out. In a population pharmacokinetic analysis, no age-related alterations in the pharmacokinetics of naldemedine were observed [see Clinical Pharmacology (12.3)].

8.6 Hepatic Impairment

The effect of severe hepatic impairment (Child-Pugh Class C) on the pharmacokinetics of naldemedine has not been evaluated. Avoid use of SYMPROIC in patients with severe hepatic impairment. No dose adjustment of SYMPROIC is required in patients with mild or moderate hepatic impairment [see Clinical Pharmacology (12.3)].

10 OVERDOSAGE

Single doses of naldemedine up to 100 mg (500 times the recommended dose) and multiple doses of up to 30 mg (150 times the recommended dose) for 10 days have been administered to healthy subjects in clinical studies. Dose-dependent increases in gastrointestinal-related adverse reactions, including abdominal pain, diarrhea, and nausea, were observed.

Single doses of naldemedine up to 3 mg (15 times the recommended dose) and multiple doses of 0.4 mg (twice the recommended dose) for 28 days have been administered to patients with OIC in clinical studies. Dose-dependent increases in gastrointestinal-related adverse reactions, including abdominal pain, diarrhea, nausea, and vomiting, were observed. Also, chills, hyperhidrosis, and dizziness were reported more frequently at 1 and 3 mg doses and hyperhidrosis at the 0.4 mg dose.

No antidote for naldemedine is known. Hemodialysis is not an effective means to remove naldemedine from the blood [see Clinical Pharmacology (12.3)].

11 DESCRIPTION

SYMPROIC (naldemedine), an opioid antagonist, contains naldemedine tosylate as the active ingredient.

The chemical name for naldemedine tosylate is: 17-(cyclopropylmethyl)-6,7-didehydro-4,5α-epoxy-3,6,14-trihydroxy-N-[2-(3-phenyl-1,2,4-oxadiazol-5-yl)propan-2-yl]morphinan-7-carboxamide 4-methylbenzenesulfonic acid.

The structural formula is:

The empirical formula for naldemedine tosylate is C32H34N4O6∙C7H8O3S and the molecular weight is 742.84.

Naldemedine tosylate is a white to light tan powder, soluble in dimethylsulfoxide and methanol, slightly soluble in alcohol and water, and independent of pH.

SYMPROIC (naldemedine) tablets for oral use contain 0.2 mg naldemedine (equivalent to 0.26 mg of naldemedine tosylate).

Excipients are: D-mannitol, croscarmellose sodium, magnesium stearate, hypromellose, talc, and yellow ferric oxide.

12 CLINICAL PHARMACOLOGY

12.1 Mechanism of Action

Naldemedine is an opioid antagonist with binding affinities for mu-, delta-, and kappa-opioid receptors. Naldemedine functions as a peripherally-acting mu-opioid receptor antagonist in tissues such as the gastrointestinal tract, thereby decreasing the constipating effects of opioids.

Naldemedine is a derivative of naltrexone to which a side chain has been added that increases the molecular weight and the polar surface area, thereby reducing its ability to cross the blood-brain barrier (BBB). Naldemedine is also a substrate of the P-glycoprotein (P-gp) efflux transporter. Based on these properties, the CNS penetration of naldemedine is expected to be negligible at the recommended dose levels, limiting the potential for interference with centrally-mediated opioid analgesia.

12.2 Pharmacodynamics

Use of opioids induces slowing of gastrointestinal motility and transit. Antagonism of gastrointestinal mu-opioid receptors by naldemedine inhibits opioid-induced delay of gastrointestinal transit time.

Effect on Cardiac Repolarization

At a dose up to 5 times the recommended dose, SYMPROIC does not prolong the QT interval to any clinically relevant extent.

12.3 Pharmacokinetics

Absorption

Following oral administration, naldemedine is absorbed with a time to achieve peak concentrations (Tmax) of approximately 0.75 hours in a fasted state. Across the range of doses evaluated, the maximum plasma concentration (Cmax) and area under the plasma concentration-time curve (AUC) increased in a dose-proportional or almost dose-proportional manner. Accumulation was minimal following multiple daily doses of naldemedine.

Food Effect

A high-fat meal decreased the rate but not the extent of naldemedine absorption. The Cmax was decreased by approximately 35% and time to achieve Cmax was delayed from 0.75 hours in the fasted state to 2.5 hours in the fed state, whereas there was no meaningful change in the AUC in the fed state [see Dosage and Administration (2.2)].

Distribution

Plasma protein binding of naldemedine in humans is 93% to 94%. The mean apparent volume of distribution during the terminal phase (Vz/F) is 155 L.

Elimination

The terminal elimination half-life of naldemedine is 11 hours.

Metabolism

Naldemedine is primarily metabolized by CYP3A to nor-naldemedine, with minor contribution from UGT1A3 to form naldemedine 3-G. Nor-naldemedine and naldemedine 3-G have been shown to have antagonistic activity for opioid receptors, with less potent effect than naldemedine.

Following oral administration of [^14C]-labeled naldemedine, the primary metabolite in plasma was nor-naldemedine, with a relative exposure compared to naldemedine of approximately 9% to 13%. Naldemedine 3-G was a minor metabolite in plasma, with a relative exposure to naldemedine of less than 3%.

Naldemedine also undergoes cleavage in the GI tract to form benzamidine and naldemedine carboxylic acid.

Excretion

Following oral administration of [^14C]-labeled naldemedine, the total amount of radioactivity excreted in the urine and feces was 57% and 35% of the administered dose of naldemedine, respectively. The amount of naldemedine excreted unchanged in the urine was approximately 16% to 18% of the administered dose. Benzamidine was the most predominant metabolite excreted in the urine and feces, representing approximately 32% and 20% of the administered dose of naldemedine, respectively. The percentage of unchanged drug in feces has not been estimated.

Use in Specific Populations

Age: Geriatric Population, Sex, Race/Ethnicity

A population pharmacokinetic analysis from clinical studies with naldemedine did not identify a clinically meaningful effect of age, sex, or race on the pharmacokinetics of naldemedine.

Renal Impairment

The pharmacokinetics of naldemedine after administration of a 0.2 mg single oral dose of SYMPROIC was studied in subjects with mild (n=8, estimated glomerular filtration rate [eGFR] of 60 to 89 mL/min/1.73 m^2), moderate (n=8, eGFR 30 to 59 mL/min/1.73 m^2), and severe (n=6, eGFR less than 30 mL/min/1.73 m^2) renal impairment, and subjects with end-stage renal disease (ESRD) requiring hemodialysis (n=8), and compared to healthy subjects with normal renal function (n=8, estimated creatinine clearance of at least 90 mL/min). The pharmacokinetics of naldemedine between subjects in all groups were similar.

Plasma concentrations of naldemedine in subjects with ESRD requiring hemodialysis were similar when SYMPROIC was administered either pre- or post-hemodialysis, indicating that naldemedine was not removed from the blood by hemodialysis.

Hepatic Impairment

The effect of hepatic impairment on the pharmacokinetics of a 0.2 mg single oral dose of SYMPROIC was studied in subjects with hepatic impairment classified as mild (n=8, Child-Pugh Class A) or moderate (n=8, Child-Pugh Class B) and compared with healthy subjects with normal hepatic function (n=8). The pharmacokinetics of naldemedine between subjects in all groups were similar.

The effect of severe hepatic impairment (Child-Pugh Class C) on the pharmacokinetics of naldemedine was not evaluated [see Use in Specific Populations (8.6)].

Drug Interaction Studies

Effect of Naldemedine on Other Drugs

In in vitro studies at clinically relevant concentrations, naldemedine did not inhibit the major CYP enzymes (including CYP1A2, CYP2A6, CYP2B6, CYP2C8, CYP2C9, CYP2C19, CYP2D6, CYP2E1, CYP3A4/5, or CYP4A11 isozymes) and is not an inhibitor of transporters (including OATP1B1, OATP1B3, OCT1, OCT2, OAT1, OAT3, BCRP, or P-gp). Naldemedine did not cause significant induction of CYP1A2, CYP2B6, CYP3A4, UGT1A2, UGT1A6, or UGT2B7 isozymes.

Effect of Other Drugs on Naldemedine

Naldemedine is primarily metabolized by the CYP3A4 enzyme with a minor contribution from UGT1A3. Naldemedine is a substrate of P-gp. The effects of co-administered drugs on the pharmacokinetics of naldemedine are summarized in Figure 1.

Figure 1: Effect of Co-Administered Drugs on the Pharmacokinetics of Naldemedine

Efavirenz (moderate CYP3A inducer): Simulation using physiologically-based pharmacokinetic modeling suggested that concomitant use of efavirenz decreases exposure to naldemedine by 43%. The clinical consequence of this decreased exposure is unknown.

No drug interaction studies have been conducted for SYMPROIC with drugs that alter gastric pH (e.g., antacids, proton-pump inhibitors).

13 NONCLINICAL TOXICOLOGY

13.1 Carcinogenesis, Mutagenesis, Impairment of Fertility

Carcinogenesis

In 2-year carcinogenicity studies, there were no drug-related neoplastic findings following oral administration of naldemedine to mice and rats at doses up to 100 mg/kg/day (approximately 17,500 and 6,300 times the human exposures (AUC) at the recommended human dose, respectively).

Mutagenesis

Naldemedine was not genotoxic in the in vitro bacterial reverse mutation (Ames) assay, a chromosomal aberration assay with cultured Chinese hamster lung cells, or an in vivo micronucleus assay with rat bone marrow cells.

Impairment of Fertility

Naldemedine was found to have no effect on fertility or reproductive performance in male and female rats at oral doses up to 1000 mg/kg/day (approximately 17,000 times the human exposures (AUC) at the recommended human dose). In female rats, prolongation of diestrous phase was noted at 10 mg/kg/day (approximately 179 times the human exposures (AUC) at the recommended human dose).

14 CLINICAL STUDIES

SYMPROIC was evaluated in two replicate, 12-week, randomized, double-blind, placebo-controlled trials (Study 1 and Study 2) in which SYMPROIC was used without laxatives in patients with OIC and chronic non-cancer pain.

Patients receiving a stable opioid morphine equivalent daily dose of at least 30 mg for at least 4 weeks before enrollment and self-reported OIC were eligible for clinical trial participation.

Patients with evidence of significant structural abnormalities of the GI tract were not enrolled in these trials.

In Studies 1 and 2, patients had to either be not using laxatives or willing to discontinue laxative use at the time of screening and willing to use only the provided rescue laxatives during the screening and treatment periods.

In Studies 1 and 2, OIC was confirmed through a two-week run in period and was defined as no more than 4 spontaneous bowel movements (SBMs) total over 14 consecutive days and less than 3 SBMs in a given week with at least 25% of the SBMs associated with one or more of the following conditions: (1) straining; (2) hard or lumpy stools; (3) having a sensation of incomplete evacuation; and (4) having a sensation of anorectal obstruction/blockage.

An SBM was defined as a bowel movement (BM) without rescue laxative taken within the past 24 hours. Patients with no BMs over the 7 consecutive days prior to and during the 2-week screening period or patients who had never taken laxatives were excluded.

In the screening and treatment periods, bisacodyl was used as rescue laxative if patients had not had a BM for 72 hours and were allowed one-time use of an enema, if after 24 hours of taking bisacodyl they still had not had a BM.

A total of 547 patients in Study 1 and 553 patients in Study 2 were randomized in a 1:1 ratio to receive SYMPROIC 0.2 mg once daily or placebo for 12 weeks. Study medication was administered without regard to meals.

The mean age of subjects in Studies 1 and 2 was 54 years; 59% were women; and 80% were white. The most common types of pain in Studies 1 and 2 were back or neck pain (61%). The mean baseline number of SBMs was 1.3 and 1.2 per week for Studies 1 and 2, respectively.

Prior to enrollment, patients were using their current opioid for a mean duration of approximately 5 years. A wide range of types of opioids were used. The mean baseline opioid morphine equivalent daily dosage was 132 mg and 121 mg per day for Studies 1 and 2, respectively.

The efficacy of SYMPROIC was assessed in Studies 1 and 2 using a responder analysis. A responder was defined as a patient who had at least 3 SBMs per week and a change from baseline of at least 1 SBM per week for at least 9 out of the 12 weeks and 3 out of the last 4 weeks in Studies 1 and 2.

The responder rates in Studies 1 and 2 are shown in Table 4.

Table 4: Efficacy Responder Rates in Studies 1 and 2 in Patients with OIC and Chronic Non-Cancer Pain
 | Study 1 |  |  | Study 2
 | SYMPROIC 0.2 mg once daily (N=273) | Placebo (N=272) | Treatment Difference [95% CI] | SYMPROIC 0.2 mg once daily (N=276) | Placebo (N=274) | Treatment Difference [95% CI]
Responder [The primary endpoint was defined as a patient who had at least 3 SBMs per week and a change from baseline of at least 1 SBM per week for at least 9 out of the 12 study weeks and 3 out of the last 4 weeks.] | 130 (48%) | 94 (35%) | 13% [5%, 21%] | 145 (53%) | 92 (34%) | 19% [11%, 27%]
p value [Cochran-Mantel-Haenszel test adjusted for opioid dose strata (30 to 100 mg; greater than 100 mg)] |  |  | 0.0020 |  |  | <0.0001
CI=Confidence Interval

In Studies 1 and 2, the mean increase in frequency of SBMs per week from baseline to the last 2 weeks of the 12-week treatment period was 3.1 for SYMPROIC vs. 2.0 for placebo (difference 1.0, 95% CI 0.6, 1.5), and 3.3 for SYMPROIC vs. 2.1 for placebo (difference 1.2, 95% CI 0.8, 1.7), respectively.

During week 1 of the treatment period, the mean increase in frequency of SBMs per week from baseline was 3.3 for SYMPROIC vs. 1.3 for placebo (difference 2.0, 95% CI 1.5, 2.5) in Study 1 and 3.7 for SYMPROIC vs. 1.6 for placebo (difference 2.1, 95% CI 1.5, 2.6) in Study 2.

The mean increase in the frequency of complete SBM (CSBM) per week from baseline to the last 2 weeks of 12-week treatment period was 2.3 for SYMPROIC vs. 1.5 for placebo (difference 0.8, 95% CI 0.4, 1.2) in Study 1 and 2.6 for SYMPROIC vs. 1.6 for placebo (difference 1.1, 95% CI 0.6, 1.5) in Study 2. A CSBM was defined as a SBM that was associated with a sense of complete evacuation.

The change in the frequency of SBMs without straining per week from baseline to the last 2 weeks of the treatment period was 1.3 for SYMPROIC vs. 0.7 for placebo (difference 0.6, 95% CI 0.2, 0.9) in Study 1 and 1.8 for SYMPROIC vs. 1.1 for placebo (difference 0.7, 95% CI 0.3, 1.2) in Study 2.

16 HOW SUPPLIED/STORAGE AND HANDLING

SYMPROIC is supplied as 0.2 mg naldemedine tablets as follows:

- bottle of 30 tablets - NDC 59385-041-30

STORAGE AND HANDLING

Store SYMPROIC in a light resistant container at 20°C to 25°C (68°F to 77°F); excursions permitted between 15°C and 30°C (59°F and 86°F) [see USP Controlled Room Temperature].

17 PATIENT COUNSELING INFORMATION

Advise the patient to read the FDA-approved patient labeling (Medication Guide).

Administration

Advise patients to discontinue SYMPROIC if treatment with the opioid pain medication is also discontinued.

Gastrointestinal Perforation

Advise patients to discontinue SYMPROIC and to promptly seek medical attention if they develop unusually severe, persistent or worsening abdominal pain [see Warnings and Precautions (5.1)].

Opioid Withdrawal

Advise patients that clusters of symptoms consistent with opioid withdrawal may occur while taking SYMPROIC and to contact their healthcare provider if these symptoms occur [see Warnings and Precautions (5.2)].

Pregnancy

Advise females of reproductive potential, who become pregnant or are planning to become pregnant, that the use of SYMPROIC during pregnancy may precipitate opioid withdrawal in a fetus due to the undeveloped blood-brain barrier [see Use in Specific Populations (8.1)].

Lactation

Advise women that breastfeeding is not recommended during treatment with SYMPROIC and for 3 days after the final dose [see Use in Specific Populations (8.2)].

SYMPROIC is a registered trademark of Shionogi & Co., Ltd.
Manufactured for: Collegium Pharmaceutical, Inc. Stoughton, MA 02072
SYM-001-PI-JULY2025

MEDICATION GUIDE
SYMPROIC® (sim proe' ik)
(naldemedine) tablets, for oral use

What is the most important information I should know about SYMPROIC?

SYMPROIC may cause serious side effects, including:

- Tear in your stomach or intestinal wall (perforation). Stomach pain that is severe can be a sign of a serious medical condition. If you get stomach pain that does not go away, stop taking SYMPROIC and get emergency medical help right away.
- Opioid withdrawal. You may have symptoms of opioid withdrawal during treatment with SYMPROIC including sweating, chills, tearing, warm or hot feeling to your face (flush), sneezing, fever, feeling cold, abdominal pain, diarrhea, nausea, and vomiting. Tell your healthcare provider if you have any of these symptoms.

What is SYMPROIC?

SYMPROIC is a prescription medicine used to treat constipation that is caused by prescription pain medicines called opioids in adults with long-lasting (chronic) pain that is not caused by active cancer.
It is not known if SYMPROIC is safe and effective in children.

Do not take SYMPROIC if you:

- have a bowel blockage (intestinal obstruction) or have a history of bowel blockage.
- are allergic to SYMPROIC or any of the ingredients in SYMPROIC. See the end of this Medication Guide for a complete list of ingredients in SYMPROIC. Tell your healthcare provider or pharmacist before you start or stop any medicines during treatment with SYMPROIC.

Before you take SYMPROIC, tell your healthcare provider about all of your medical conditions, including if you:

- have any stomach or bowel (intestines) problems, including, cancer or past surgery of the stomach or bowel, diverticulitis, or had chemotherapy or radiation treatment..
- have liver problems.
- are pregnant or plan to become pregnant. Taking SYMPROIC during pregnancy may cause opioid withdrawal symptoms in your unborn baby. Tell your healthcare provider right away if you become pregnant during treatment with SYMPROIC.
- are breastfeeding or plan to breastfeed. It is not known if SYMPROIC passes into your breast milk. You should not breastfeed during treatment with SYMPROIC and for 3 days after your last dose. Taking SYMPROIC while you are breastfeeding may cause opioid withdrawal symptoms in your baby. You and your healthcare provider should decide if you will take SYMPROIC or breastfeed. You should not do both.

Tell your healthcare provider about all the medicines you take, including prescription and over-the-counter medicines, vitamins, and herbal supplements. Other medicines may affect the way SYMPROIC works.

How should I take SYMPROIC?

- Take SYMPROIC exactly as your healthcare provider tells you to take it.
- Take your prescribed dose of SYMPROIC 1 time each day.
- SYMPROIC can be taken with or without food.
- SYMPROIC has been shown to be effective in people who have taken opioid pain medicines for at least 4 weeks.
- Tell your healthcare provider if you stop taking your opioid pain medicine. If you stop taking your opioid pain medicine, you should also stop taking SYMPROIC.

What are the possible side effects of SYMPROIC?

See "What is the most important information I should know about SYMPROIC?"

The most common side effects of SYMPROIC include stomach (abdomen) pain, diarrhea, nausea and vomiting (gastroenteritis).
Tell your healthcare provider if you have any side effect that bothers you or that does not go away. These are not all the possible side effects of SYMPROIC. Call your doctor for medical advice about side effects. You may report side effects to FDA at 1-800-FDA-1088.

How should I store SYMPROIC?

- Store SYMPROIC at room temperature between 68°F to 77°F (20°C to 25°C).
- Keep SYMPROIC in the bottle that it comes in.

Keep SYMPROIC and all medicines out of the reach of children.

General information about the safe and effective use of SYMPROIC.

Medicines are sometimes prescribed for purposes other than those in a Medication Guide. Do not take SYMPROIC for a condition for which it was not prescribed. Do not give SYMPROIC to other people, even if they have the same symptoms that you have. It may harm them. You can ask your pharmacist or healthcare provider for information about SYMPROIC that is written for health professionals.

What are the ingredients in SYMPROIC?

Active Ingredient: naldemedine tosylate

Inactive ingredients: D-mannitol, croscarmellose sodium, magnesium stearate, hypromellose, talc, and yellow ferric oxide.
Manufactured for: Collegium Pharmaceutical, Inc. Stoughton, MA 02072

SYM-001-MG-JULY2025
SYMPROIC is a registered trademark of Shionogi & Co., Ltd. For more information, go to www.symproic.com or call 1-800-469-0261.

This Medication Guide has been approved by the U.S. Food and Drug Administration.

Revised: 07/2025

PRINCIPAL DISPLAY PANEL - 0.2 mg Tablet Bottle Label - 30 Tablets

NDC 59385-041-30
Rx ONLY
30 Tablets

Symproic®
(naldemedine) tablets
0.2 mg

Dispense the enclosed Medication Guide
to each patient.

Collegium®
PHARMACEUTICAL

© 2023 Collegium Pharmaceutical, Inc.
Stoughton, MA 02072

PRINCIPAL DISPLAY PANEL - 0.2 mg Tablet Blister Pack

7 Tablets
Each tablet contains 0.2 mg of naldemedine
(equivalent to 0.26 mg of naldemedine tosylate).
Usual adult dosage: See package insert.

Store at 20°C to 25°C (68°F to 77°F).

Mfd. for BioDelivery Sciences International, Inc.
Raleigh, NC 27612

Symproic®
(naldemedine) tablets
0.2 mg

NDC 59385-041-07 Rx ONLY

Keep out of reach of children.
PHYSICIAN SAMPLES NOT FOR SALE
319623 04/19 SYM-0001.1b

DAY 1
DAY 2
DAY 3
DAY 4
DAY 5
DAY 6
DAY 7

LOT:
EXP:

PRINCIPAL DISPLAY PANEL - 0.2 mg Tablet Blister Pack Carton

NDC 59385-041-07

7 Tablets
Dosage: Take 1 tablet
once daily

Each tablet contains 0.2 mg of
naldemedine (equivalent to
0.26 mg of naldemedine tosylate).

Please see the included
Prescribing Information.

Keep out of reach of children.

Dispense the enclosed Medication Guide
to each patient.

Symproic®
(naldemedine) tablets
0.2 mg

PHYSICIAN SAMPLES NOT FOR SALE
FOR ORAL USE ONLY
Rx ONLY